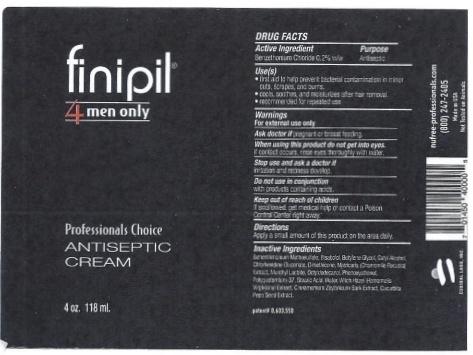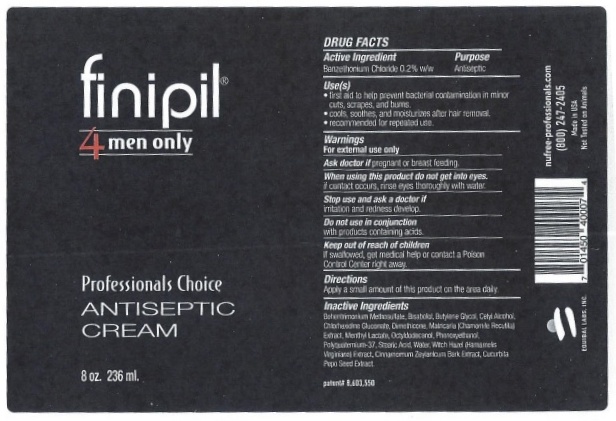 DRUG LABEL: finipil 4 men only
NDC: 53228-231 | Form: LIQUID
Manufacturer: Equibal, Inc.
Category: otc | Type: HUMAN OTC DRUG LABEL
Date: 20251217

ACTIVE INGREDIENTS: BENZETHONIUM CHLORIDE 200 mg/1000 mg
INACTIVE INGREDIENTS: CETYL ALCOHOL

finipil 4 men only

Active Ingredient

Benzethonium Chloride 0.2% w/w

Purpose

Antiseptic

Keep out of reach of children

if swallowed, get medical help or contact a Poison Control Center right away.

Indications & Usage

Uses(s)

- first aid to help prevent bacterial contamination in minor cuts, scrapes, and burns.
- cools, soothes, and moisturizes after hair removal.
- recommended for repeated use.

Warnings

For external use only

Ask a doctor ifpregnant or breast feeding.

When Using product

When using this product do not get into eyes.

if contact occurs, rinse eyes thoroughly with water.

Stop Use

Stop use and ask a doctor if

irritation and redness develop

Other Safety Information

Do not use in conjunction

with products containing acids.

Dosage & Administration

Directions

Apply a small amount of this product on the area daily.

Inactive Ingredients

Bethecrimium methosulfate, Bisabolol, Betylene Glycol, Cetyle Alcohol, Chlorhexidine Gluconate, Dimethicone, Matricaria (Chamomile Recutital) Extract, Menthyl Lactate, Octylodecanoil, Phenoxyethanol, Phenoxyethanol, Polyquaterniuim-37, Stearic Acid, Water, Witch Hazel (Hamamelis Virginiana) Extract, Cinnacrium Zeyarcium Bark Extract, Cucurbita Pepo Seed Extract

Package label 4 oz

finipil®

4 men only

Professionals Choice

ANTISEPTIC CREAM

4 oz. 118 ml

DRUG FACTS

Active Ingredient Purpose

Benzethonium Chloride 0.2% w/w Antiseptic

Uses(s)

- first aid to help prevent bacterial contamination in minor cuts, scrapes, and burns.
- cools, soothes, and moisturizes after hair removal.
- recommended for repeated use.

Warnings

For external use only

Ask a doctor ifpregnant or breast feeding.

When using this product do not get into eyes

if contact occurs, rinse eyes thoroughly with water.

Stop use and ask a doctor if

irritation and redness develop

Do not use in conjunction

with products containing acids.

Keep out of reach of children

if swallowed, get medical help or contact a Poison Control Center right away.

Directions

Apply a small amount of this product on the area daily.

Inactive Ingredients

Bethecrimium methosulfate, Bisabolol, Betylene Glycol, Cetyle Alcohol, Chlorhexidine Gluconate, Dimethicone, Matricaria (Chamomile Recutital) Extract, Menthyl Lactate, Octylodecanoil, Phenoxyethanol, Phenoxyethanol, Polyquaterniuim-37, Stearic Acid, Water, Witch Hazel (Hamamelis Virginiana) Extract, Cinnacrium Zeyarcium Bark Extract, Cucurbita Pepo Seed Extract

Patent # 603,550

EQUIBAL LABS, INC.

Nufree-professionals.com

(800) 247-2405

Made in USA

Not Tested on Animals

Package label 8 oz

finipil®

4 men only

Professionals Choice

ANTISEPTIC CREAM

8 oz. 236 ml

DRUG FACTS

Active Ingredient Purpose

Benzethonium Chloride 0.2% w/w Antiseptic

Uses(s)

- first aid to help prevent bacterial contamination in minor cuts, scrapes, and burns.
- cools, soothes, and moisturizes after hair removal.
- recommended for repeated use.

Warnings

For external use only

Ask a doctor ifpregnant or breast feeding.

When using this product do not get into eyes.

if contact occurs, rinse eyes thoroughly with water.

Stop use and ask a doctor if

irritation and redness develop

Do not use in conjunction

with products containing acids.

Keep out of reach of children

if swallowed, get medical help or contact a Poison Control Center right away.

Directions

Apply a small amount of this product on the area daily.

Inactive Ingredients

Bethecrimium methosulfate, Bisabolol, Betylene Glycol, Cetyle Alcohol, Chlorhexidine Gluconate, Dimethicone, Matricaria (Chamomile Recutital) Extract, Menthyl Lactate, Octylodecanoil, Phenoxyethanol, Phenoxyethanol, Polyquaterniuim-37, Stearic Acid, Water, Witch Hazel (Hamamelis Virginiana) Extract, Cinnacrium Zeyarcium Bark Extract, Cucurbita Pepo Seed Extract

Patent # 603,550

EQUIBAL LABS, INC.

Nufree-professionals.com

(800) 247-2405

Made in USA

Not Tested on Animals